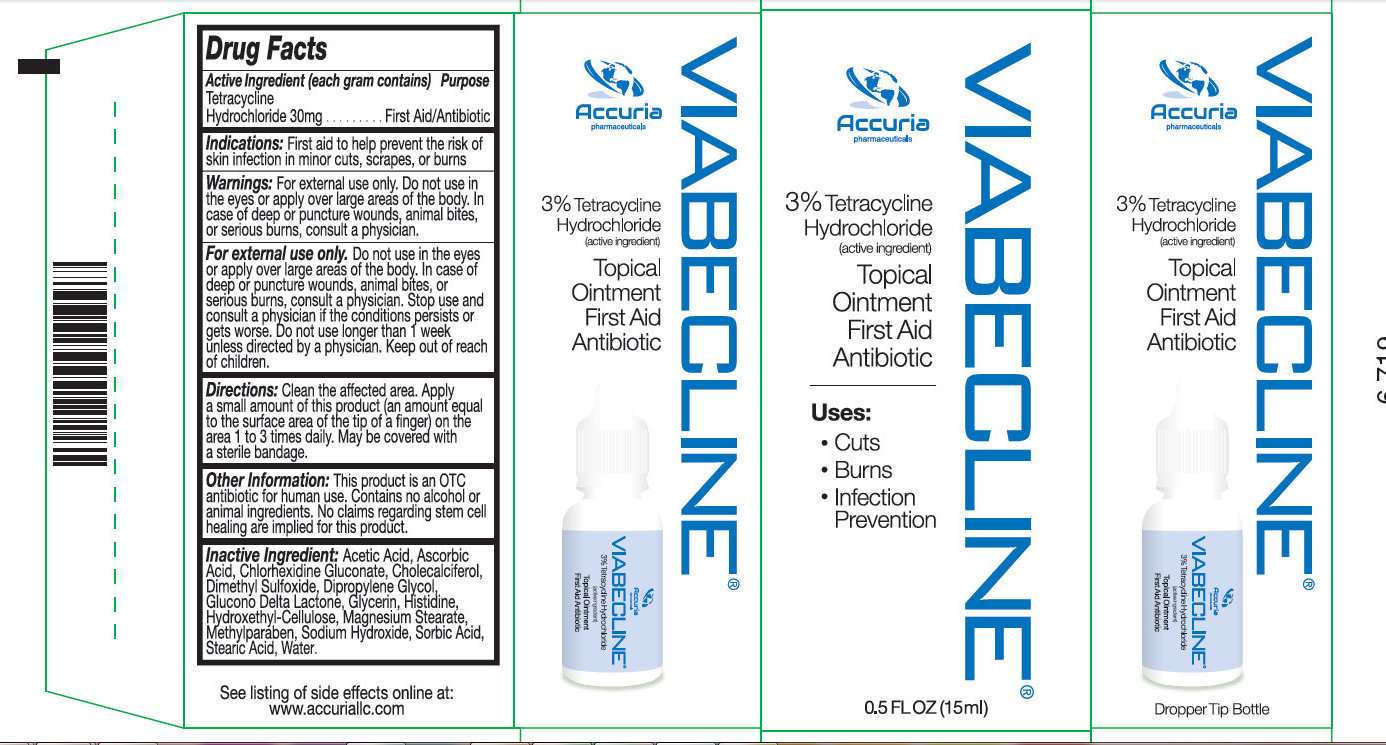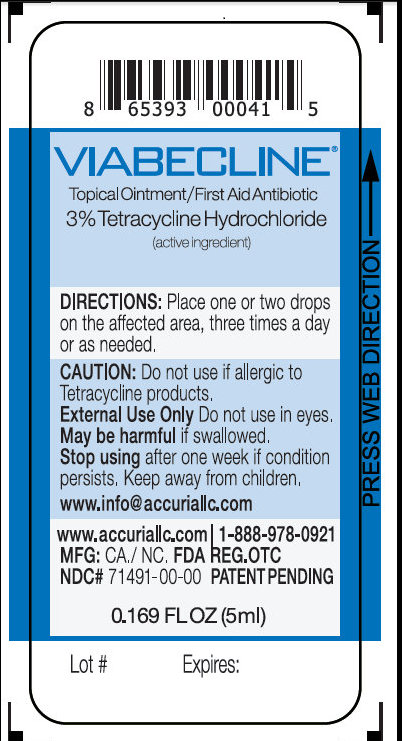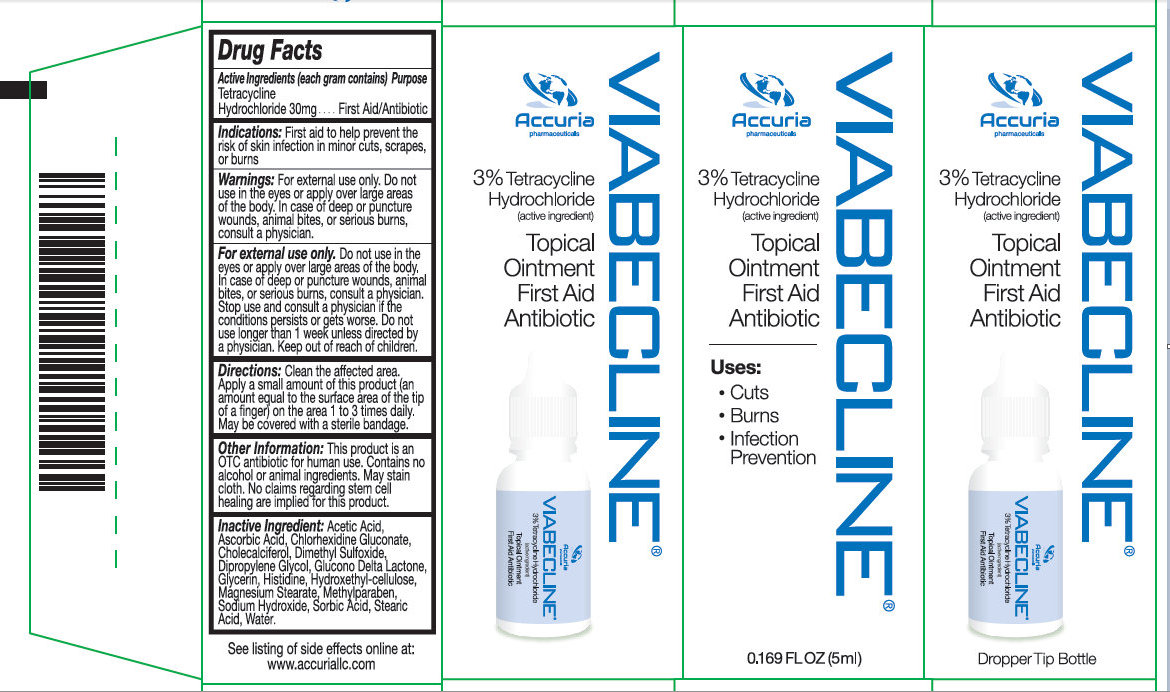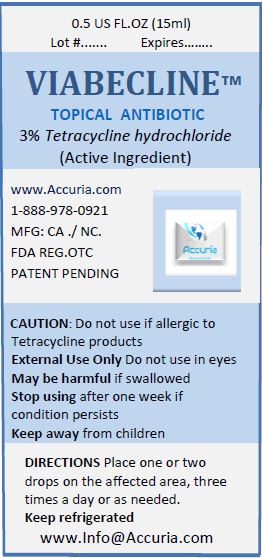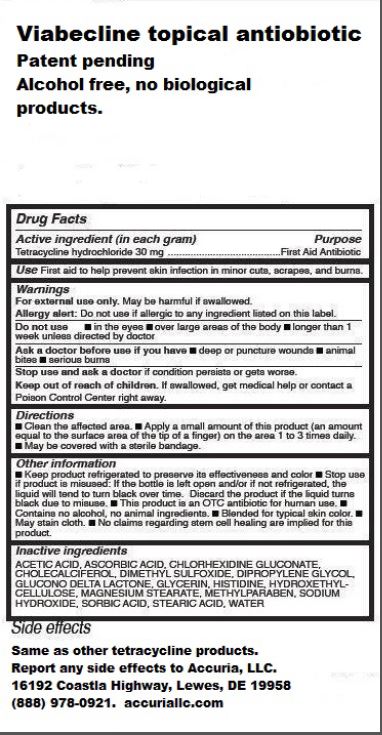 DRUG LABEL: Viabecline
NDC: 71491-100 | Form: OINTMENT
Manufacturer: Accuria, LLC
Category: otc | Type: HUMAN OTC DRUG LABEL
Date: 20231201

ACTIVE INGREDIENTS: TETRACYCLINE HYDROCHLORIDE 30 mg/1 mL
INACTIVE INGREDIENTS: ACETIC ACID; ASCORBIC ACID; CHLORHEXIDINE GLUCONATE; CHOLECALCIFEROL; DIMETHYL SULFOXIDE; DIPROPYLENE GLYCOL; GLUCONOLACTONE; GLYCERIN; HISTIDINE; HYDROXYMETHYL CELLULOSE; MAGNESIUM STEARATE; METHYLPARABEN; SODIUM HYDROXIDE; SORBIC ACID; STEARIC ACID; WATER

Viabecline

Activer Ingredient (in each gram)

Tetracycline Hydrochloride 30 mg

Purpose

First Aid Antibiotic

Use

First aid to help prevent skin infection in minor cuts, scrapes, and burns.

Warnings

May be harmful if swallowed. For external use only.

Do not use if allergic to any ingredient listed on this label. Allergy Alert:

Do not use

Ask doctor before use if you have

Stop use and ask a doctor if the condition persists or gets worse.

- in the eyes
- over large areas of the body
- longer than 1 week unless directed by a doctor

- deep or puncture wounds
- animal bites
- serious burns

KEEP OUT OF REACH OF CHILDREN

If swallowed, get medical help or contact a poison Control Center right away. Keep out of reach of children.

Directions

- Clean the affected area
- Apply a small amount of this product (an amount equal to the surface area of the tip of a finger) on the area 1 to 3 times daily.
- May be covered with a sterile bandage.

Other information

- Keep product refrigerated to preserve its effectiveness and color
- Stop use if the product is misused: If the bottle is left open and or not refrigerated, the liquid will tend to turn black over time. Discard the product if the liquid turns black due to misuse.
- This product is an OTC antibiotic for human use.
- Contains no alcohol, no animal ingredients.
- Blended for typical skin color.
- May stain cloth.
- No claims regarding stem cell healing are implied for this product.

Inactive Ingredients

ACETIC ACID, ASCORBIC ACID, CHLORHEXIDINE GLUCONATE, CHOLECALCIFEROL, DIMETHYL SULFOXIDE, DIPROPYLENE GLYCOL, GLUCONO DELTA LACTONE, GLYCERIN, HISTIDINE, HYDROXETHYL-CELLULOSE, MAGNESIUM STEARATE, METHYLPARABEN, SODIUM HYDROXIDE, SORBIC ACID, STEARIC ACID, WATER